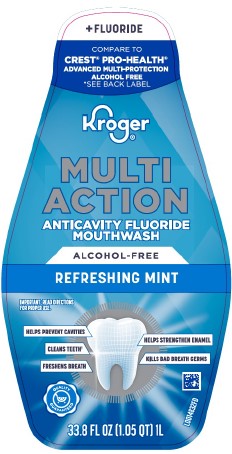 DRUG LABEL: Oral Antivavity
NDC: 30142-576 | Form: MOUTHWASH
Manufacturer: The Kroger Co.
Category: otc | Type: HUMAN OTC DRUG LABEL
Date: 20260227

ACTIVE INGREDIENTS: SODIUM FLUORIDE 10.41 mg/1 mL
INACTIVE INGREDIENTS: GLYCERIN; CETYLPYRIDINIUM CHLORIDE; SACCHARIN SODIUM; PHOSPHORIC ACID; SODIUM BENZOATE; SUCRALOSE; WATER; POLOXAMER 407; BENZOIC ACID; SODIUM PHOSPHATE, DIBASIC, ANHYDROUS; PROPYLENE GLYCOL; FD&C BLUE NO. 1

Kroger 576.001/576AD
Alcohol Free Fluoride Refreshing Mint Mouthwash

TEP

SEALED WITH PRINTED NECKBAND FOR YOUR PROTECTION

claims

Kroger ®

MULTI

ACTION

ANTICAVITY FLUORIDE MOUTHWASH

Active ingredient

Sodium fluoride 0.02% (0.01% w/v fluoride ion)

Purpose

Anticavity

Use

aids in the prevention of dental cavities

Warnings

For this product

Keep out of reach of children

If more than used for rinsing is accidentally swallowed, get medical help or contact a Poison Control Center Right Away

Directions

Adults and children 6 years of age and older:

- use twice a day after brushing your teeth with a toothpaste
- vigorously swish 10 mL (2 teaspoonfuls) of rinse between your teeth for 1 minute then spit out
- do not swallow the rinse
- do not eat or drink for 30 minutes after rinsing
- instruct children under 12 years of age in good rinsing habits (to minimize swallowing)
- supervise children as necessary until capable of using witout supervision
- children under 6 years of age: consult a dentist or doctor

Inactive ingredients

water, glycerin, flavor, cetylpyridinium chloride, sodium saccharin, phosphoric acid, sodium benzoate, sucralose, poloxamer 407, benzoic acid, disodium phosphate, propylene glycol, blue 1

Questions or comments?

1-800-632-6900

Disclaimer

†THIS PRODUCT IS NOT INTENDED TO REPLACE BRUSHING OR FLOSSING

THIS RINSE MAY CAUSE TEMPORARY STAINING TO THE SURFACE OF TEETH.

THIS IS NOT HARMFUL, AND ADEQUATE BRUSHING MAY PREVENT ITS OCCURRENCE.

*THIS PRODUCT IS NOT MANUFACTURED OR DISTRIBUTED BY PROTECTER & GAMBLE, DISTRIBUTOR OF CREST ®PRO-HEALTH MULTI-PROTECTION ALCOHOL FREE RINSE.

Adverse Reactions

PROUDLY DISTRIBUTED BY THE KROGER CO., CINCINNATI, OHIO 452020

MADE IN USA WITH US AND FOREIGN COMPONENTS

Quality Guaranteed

Kroger.com/guarantee

800-632-6900

principal display panel

+ FLUORIDE

COMPARE TO

CREST ®PRO-HEALTH ®

ADVANCED MULTI-PROTECTION

ALCOHOL FREE

*See Back Label

Kroger ®

MULTI

ACTION

ANTICAVITY FLUORIDE

MOUTHWASH

IMPORTANT: READ DIRECTIONS FOR PROPER USE.

HELPS PREVENT CAVITIES

CLEANS TEETH†

FRESHENS BREATH

HELPS STRENGTHEN ENAMEL

KILLS BAD BREATH GERMS

QUALITY GUARANTEED

33.8 FL OZ (1.05 QT) 1L